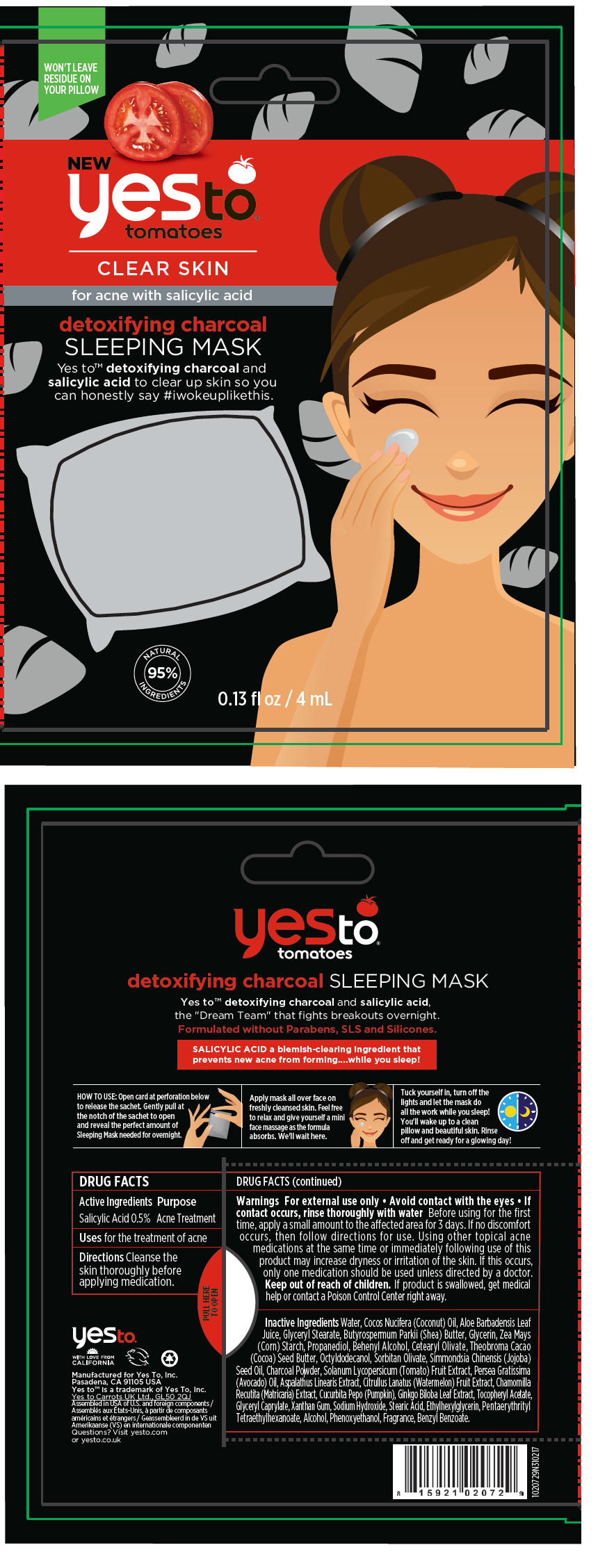 DRUG LABEL: Yes To Tomatoes Detoxifying Charcoal Sleeping Mask
NDC: 69840-008 | Form: CREAM
Manufacturer: Yes To Incorporated
Category: otc | Type: HUMAN OTC DRUG LABEL
Date: 20231219

ACTIVE INGREDIENTS: Salicylic Acid 5 mg/1 mL
INACTIVE INGREDIENTS: WATER; Glyceryl Stearate SE; Shea Butter; Cetostearyl Alcohol; GLYCERIN; Modified Corn Starch (1-Octenyl Succinic Anhydride); Cocoa Butter; OCTYLDODECANOL; SORBITAN OLIVATE; Jojoba Oil; GLYCERYL MONOCAPRYLOCAPRATE; STEARIC ACID; AVOCADO OIL; PROPANEDIOL; Docosanol; ALOE VERA LEAF; XANTHAN GUM; ACTIVATED CHARCOAL; WATERMELON; Alcohol; Lentil; SOLANUM LYCOPERSICUM FRUITING TOP; GINKGO; CUCURBITA PEPO WHOLE; ASPALATHUS LINEARIS WHOLE; PHENOXYETHANOL; .Alpha.-Tocopherol Acetate; MATRICARIA CHAMOMILLA FLOWERING TOP; ETHYLHEXYLGLYCERIN; PENTAERYTHRITYL TETRAETHYLHEXANOATE; SODIUM HYDROXIDE

Yes To® Tomatoes Detoxifying Charcoal Sleeping Mask

DRUG FACTS

Active Ingredients

Salicylic Acid 0.5%

Purpose

Acne Treatment

Uses

for the treatment of acne

Directions

Cleanse the skin thoroughly before applying medication.

Warnings

For external use only

- Avoid contact with the eyes
- If contact occurs, rinse thoroughly with water

Before using for the first time, apply a small amount to the affected area for 3 days. If no discomfort occurs, then follow directions for use. Using other topical acne medications at the same time or immediately following use of this product may increase dryness or irritation of the skin. If this occurs, only one medication should be used unless directed by a doctor.

Keep out of reach of children. If product is swallowed, get medical help or contact a Poison Control Center right away.

Inactive Ingredients

Water, Cocos Nucifera (Coconut) Oil, Aloe Barbadensis Leaf Juice, Glyceryl Stearate, Butyrospermum Parkii (Shea) Butter, Glycerin, Zea Mays (Corn) Starch, Propanediol, Behenyl Alcohol, Cetearyl Olivate, Theobroma Cacao (Cocoa) Seed Butter, Octyldodecanol, Sorbitan Olivate, Simmondsia Chinensis (Jojoba) Seed Oil, Charcoal Powder, Solanum Lycopersicum (Tomato) Fruit Extract, Persea Gratissima (Avocado) Oil, Aspalathus Linearis Extract, Citrullus Lanatus (Watermelon) Fruit Extract, Chamomilla Recutita (Matricaria) Extract, Cucurbita Pepo (Pumpkin), Ginkgo Biloba Leaf Extract, Tocopheryl Acetate, Glyceryl Caprylate, Xanthan Gum, Sodium Hydroxide, Stearic Acid, Ethylhexylglycerin, Pentaerythrityl Tetraethylhexanoate, Alcohol, Phenoxyethanol, Fragrance, Benzyl Benzoate.

Questions?

Visit yesto.com or yesto.co.uk

PRINCIPAL DISPLAY PANEL - 4 mL Bag Card

WON'T LEAVE
RESIDUE ON
YOUR PILLOW

NEW
yesto®
tomatoes

CLEAR SKIN

for acne with salicylic acid

detoxifying charcoal
SLEEPING MASK

Yes to™ detoxifying charcoal and
salicylic acid to clear up skin so you
can honestly say #iwokeuplikethis.

NATURAL
95%
INGREDIENTS

0.13 fl oz / 4 mL